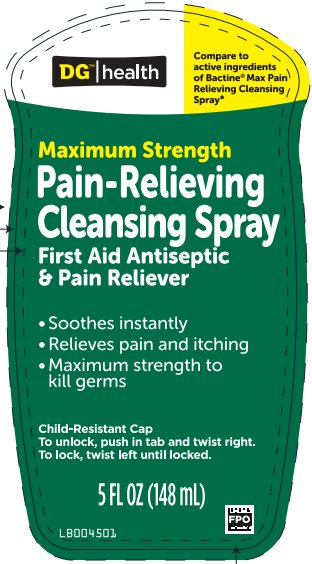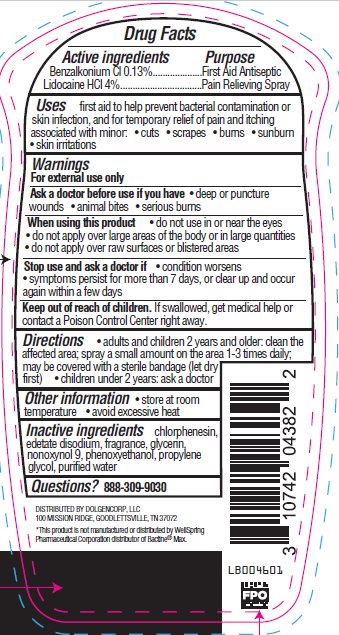 DRUG LABEL: DG Health
NDC: 75712-200 | Form: SPRAY
Manufacturer: Dollar General Corporation
Category: otc | Type: HUMAN OTC DRUG LABEL
Date: 20241217

ACTIVE INGREDIENTS: BENZALKONIUM CHLORIDE 1.3 mg/1 mL; LIDOCAINE HYDROCHLORIDE 40 mg/1 mL
INACTIVE INGREDIENTS: CHLORPHENESIN; EDETATE DISODIUM; GLYCERIN; NONOXYNOL-9; PHENOXYETHANOL; PROPYLENE GLYCOL; WATER

Drug Facts - DG Health Maximum Strength Pain Relieving Cleansing

Active ingredients

Benzalkonium Cl 0.13%

Lidocaine HCl 4%

Purpose

Benzalkonium Cl – First Aid Antiseptic

Lidocaine HCl – Pain Relieving Spray

Uses

first aid to help prevent bacterial contamination or skin infection, and for temporary relief of pain and itching associated with minor:

- cuts
- scrapes
- burns
- sunburn
- skin irritations

Warnings

For external use only

Ask a doctor before use if you have

- deep or puncture wounds
- animal bites
- serious burns

When using this product

- do not use in or near the eyes
- do not apply over large areas of the body or in large quantities
- do not apply over raw surfaces or blistered areas

Stop use and ask a doctor if

- condition worsens
- symptoms persist for more than 7 days, or clear up and occur again within a few days

Keep out of reach of children.

If swallowed, get medical help or contact a Poison Control Center right away.

Directions

- adults and children 2 years and older: clean the affected area; spray a small amount on the area 1-3 times daily; may be covered with a sterile bandage (let dry first)
- children under 2 years: ask a doctor

Other Safety Information

- store at room temperature
- avoid excessive heat

Inactive ingredients

chlorphenesin, edetate disodium, fragrance, glycerin, nonoxynol 9, phenoxyethanol, propylene glycol, purified water

Questions

888-309-9030